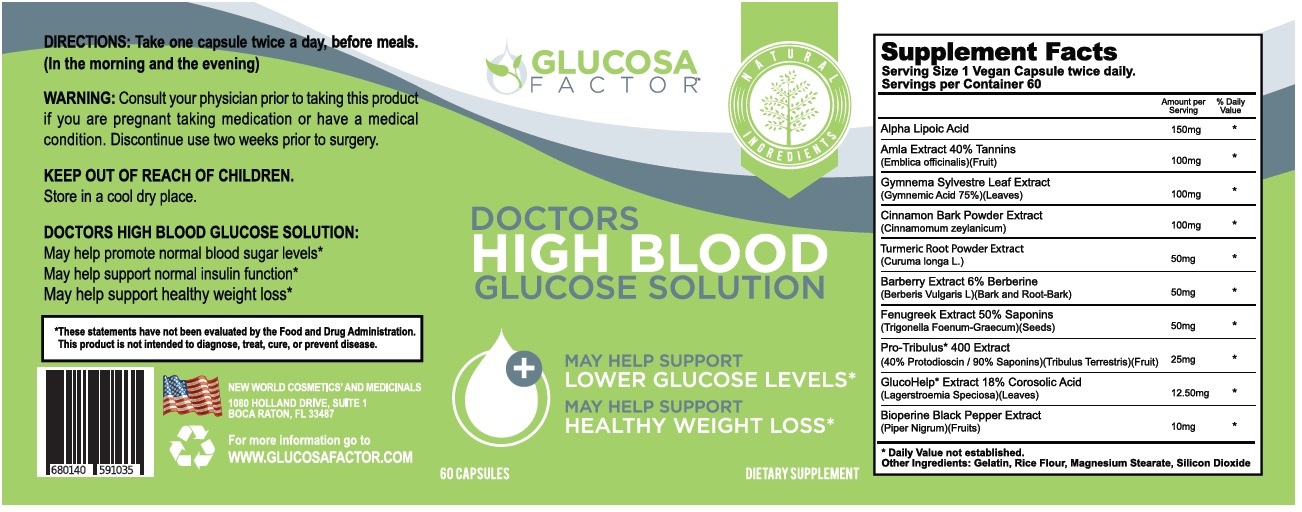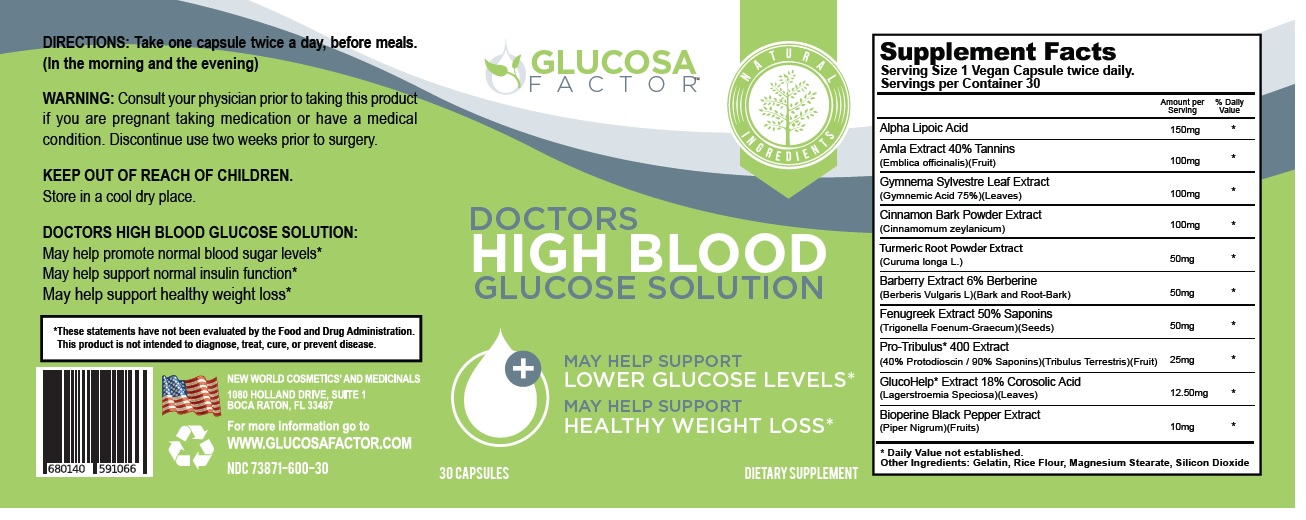 DRUG LABEL: GLUCOSA FACTOR
NDC: 73871-600 | Form: CAPSULE
Manufacturer: New World Holdings, Inc.
Category: other | Type: DIETARY SUPPLEMENT
Date: 20200418

ACTIVE INGREDIENTS: ALPHA LIPOIC ACID 150 mg/1 1; PHYLLANTHUS EMBLICA FRUIT 100 mg/1 1; GYMNEMA SYLVESTRE LEAF 100 mg/1 1; CINNAMON 100 mg/1 1; TURMERIC 50 mg/1 1; BERBERIS VULGARIS ROOT BARK 50 mg/1 1; FENUGREEK SEED 50 mg/1 1; TRIBULUS TERRESTRIS FRUIT 25 mg/1 1; LAGERSTROEMIA SPECIOSA LEAF 12.50 mg/1 1; BLACK PEPPER 10 mg/1 1
INACTIVE INGREDIENTS: GELATIN, UNSPECIFIED; BROWN RICE; MAGNESIUM STEARATE; SILICON DIOXIDE

GLUCOSA FACTOR

STATEMENT OF IDENTITY

Supplement Facts
Serving Size 1 Vegan Capsule twice daily.
Servings per Container 60
 | Amount per serving | % Daily value
Alpha Lipoic Acid | 150mg | *
Amla Extract 40% Tannins (Emblica officinalis)(Fruit) | 100mg | *
Gymnema Sylvestre Leaf Extract (Gymnemic Acid 75%)(Leaves) | 100mg | *
Cinnamon Bark Powder Extract (Cinnamomum zeylanicum) | 100mg | *
Turmeric Root Powder Extract (Curuma longa L.) | 50mg | *
Barberry Extract 6% Berberine (Berberis Vulgaris L)(Bark and Root-Bark) | 50mg | *
Fenugreek Extract 50% Saponins (Trigonella Foenum-Graecum)(Seeds) | 50mg | *
Pro-Tribulus* 400 Extract (40% Protodioscin / 90% Saponins)(Tribulus Terrestris)(Fruit) | 25mg | *
GlucoHelp* Extract 18% Corosolic Acid (Lagerstroemia Speciosa)(Leaves) | 12.50mg | *
Bioperine Black Pepper Extract (Piper Nigrum)(Fruits) | 10mg | *
* Daily value not established. Other Ingredients: Gelatin, Rice Flour, Magnesium Stearate, Silicon Dioxide

DOSAGE AND ADMINISTRATION

DIRECTIONS: Take one capsule twice a day, before meals. (In the morning and the evening)

WARNINGS

WARNING: Consult your physician prior to taking this product if you are pregnant taking medication or have a medical condition. Discontinue use two weeks prior to surgery.

KEEP OUT OF REACH OF CHILDREN.

Store in a cool dry place.

DOCTORS HIGH BLOOD GLUCOSE SOLUTION:

May help promote normal blood sugar levels*

May help support normal insulin function*

May help support healthy weight loss*

*These statements have not been evaluated by the Food and Drug Administration.

This product is not intended to diagnose, treat, cure, or prevent disease.

NATURAL INGREDIENTS

DOCTORS HIGH BLOOD GLUCOSE SOLUTION

DIETARY SUPPLEMENT

NEW WORLD COSMETICS' AND MEDICINALS

1080 HOLLAND DRIVE, SUITE 1

BOCA RATON, FL 33487

For more information go to

WWW.GLUCOSAFACTOR.COM